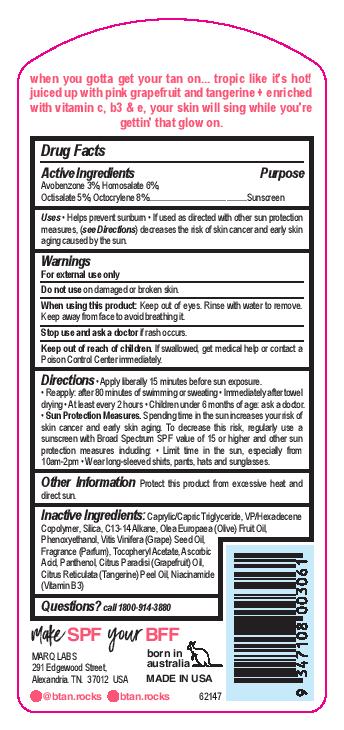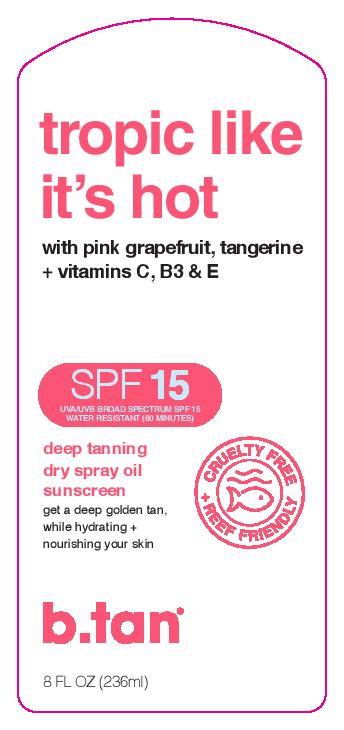 DRUG LABEL: b.tan Tropic Like Its Hot
NDC: 73978-005 | Form: SPRAY
Manufacturer: Marque of Brands Americas, LLC
Category: otc | Type: HUMAN OTC DRUG LABEL
Date: 20250101

ACTIVE INGREDIENTS: AVOBENZONE 3 mg/100 g; HOMOSALATE 6 mg/100 g; OCTISALATE 5 mg/100 g; OCTOCRYLENE 8 mg/100 g
INACTIVE INGREDIENTS: MEDIUM-CHAIN TRIGLYCERIDES; GRAPE SEED OIL; PANTHENOL; VINYLPYRROLIDONE/EICOSENE COPOLYMER; ALPHA-TOCOPHEROL ACETATE; ASCORBIC ACID; OLIVE OIL; GRAPEFRUIT OIL; MANDARIN OIL; NIACINAMIDE; C13-15 ALKANE; PHENOXYETHANOL; SILICON DIOXIDE

b.tan Tropic Like It's Hot SPF 15

ACTIVE INGREDIENT

Avobenzone 3%, Homosalate 6%, Octisalate 5%, Octocrylene 8%

PURPOSE

Sunscreen

INDICATIONS AND USAGE

- Helps prevent sunburn
- If used as directed with other sun protection measures, (see Directions) decreases the risk of skin cancer and early skin aging caused by the sun.

WARNINGS

For external use only

Do not use on damaged or broken skin.

When using this product: Keep out of eyes. Rinse with water to remove. Keep away from face to avoid breathing it.

Stop use and ask a doctor if rash occurs.

Keep out of reach of children. If swallowed, get medical help or contact a Poison Control Center immediately.

Directions

- Apple liberally 15 minutes before sun exposure.
- Reapply: after 80 minutes of swimming or sweating
- Immediately after towel drying
- At least every 2 hours
- Children under 6 months of age: ask a doctor.
- Sun Protection Measures.
- Spending time in the sun increases your risk of skin cancer and early skin aging. To decrease this risk, regularly use a sunscreen Broad Spectrum SPF value of 15 or higher and other sun protection measures including:
- Limit time in the sun, especially from 10am-2pm
- Wear long-sleeved shirts, pants, hats and sunglasses.

OTHER SAFETY INFORMATION

Protect this product from excessive heat and direct sun.

INACTIVE INGREDIENT

Caprylic/ Capric Triglyceride, VP/Hexadecene Copolymer, Silica, C13-14 Alkane, Olea Europaea (Olive) Fruit Oil, Phenoxyethanol, Vitis Vinifera (Grape) Seed Oil, Fragrance (Parfum), Tocopheryl Acetate, Ascorbic Acid, Panthenol, Citrus Paradisi (Grapefruit) Oil, Citrus Reticulata (Tangerine) Peel Oil, Niacinamide (Vitamin B3)

QUESTIONS

call 1800-914-3880